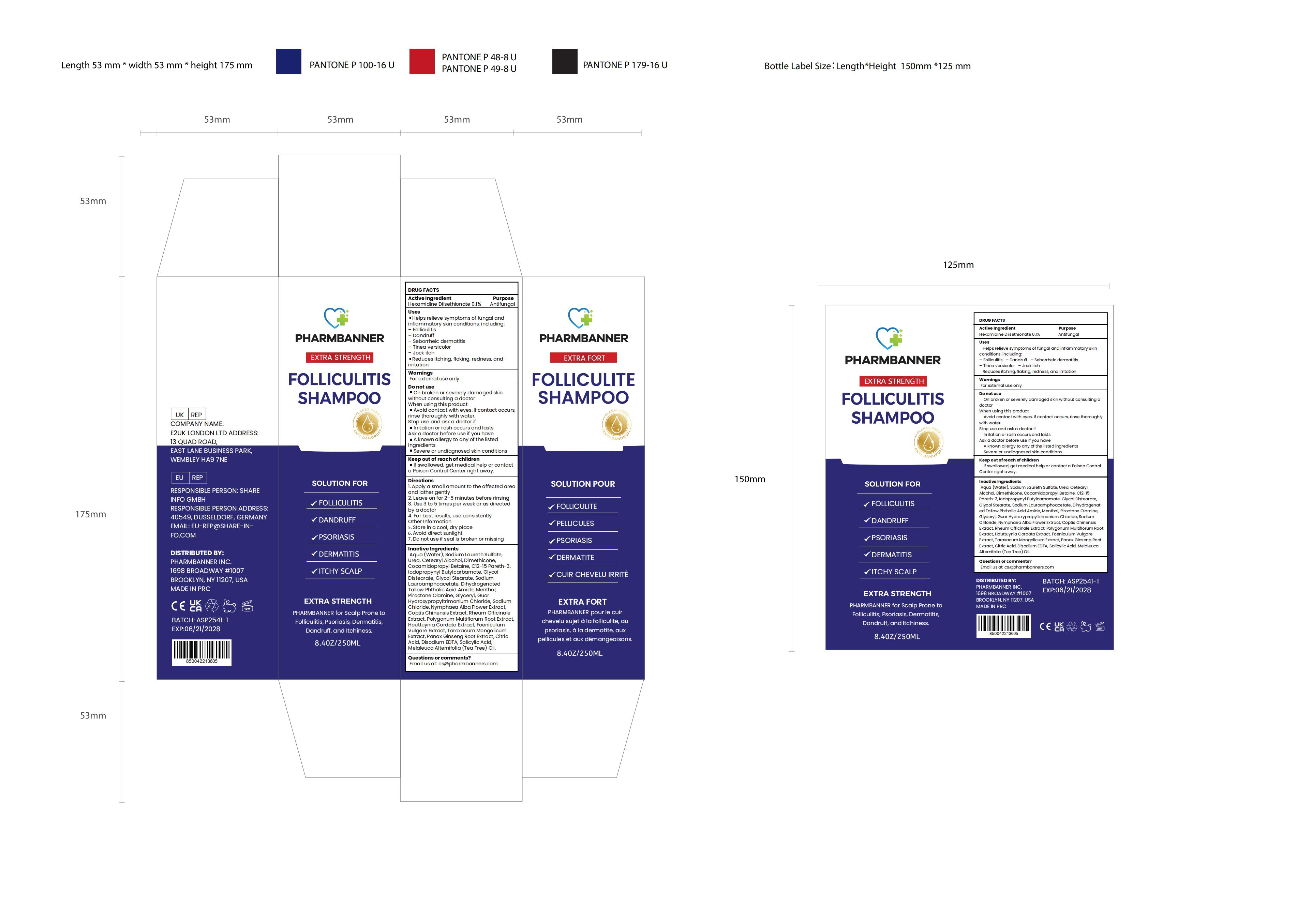 DRUG LABEL: PHARMBANNER Anti-Fungal Shampoo.
NDC: 83818-015 | Form: SHAMPOO
Manufacturer: Shenzhen Xinxin Yunhai Technology Co., Ltd.
Category: otc | Type: HUMAN OTC DRUG LABEL
Date: 20250623

ACTIVE INGREDIENTS: HEXAMIDINE DIISETHIONATE 0.1 g/100 mL
INACTIVE INGREDIENTS: SODIUM LAURETH SULFATE; UREA; C12-15 PARETH-3; IODOPROPYNYL BUTYLCARBAMATE; PIROCTONE OLAMINE; RHEUM OFFICINALE ROOT; POLYGONUM ARENASTRUM WHOLE; HOUTTUYNIA CORDATA TOP; FOENICULUM VULGARE ROOT; TARAXACUM MONGOLICUM; CITRIC ACID; MELALEUCA ALTERNIFOLIA (TEA TREE) LEAF OIL; SODIUM LAUROAMPHOACETATE; COCAMIDOPROPYL BETAINE; SODIUM CHLORIDE; NYMPHAEA ALBA FLOWER; EDETATE DISODIUM; SALICYLIC ACID; GLYCOL STEARATE; PANAX GINSENG ROOT; COPTIS CHINENSIS WHOLE; DIMETHICONE; GLYCERYL 1,3-DI(5-HYDROXYDECANOATE); WATER; CETOSTEARYL ALCOHOL; GLYCOL DISTEARATE; DIHYDROGENATED TALLOW PHTHALIC ACID AMIDE; MENTHOL; GUAR HYDROXYPROPYLTRIMONIUM CHLORIDE

83818-015

Active Ingredient

HEXAMIDINE DIISETHIONATE 0.1%

Purpose

Antifungal

Use

▪ Helps relieve symptoms of fungal and inflammatory skin conditions, including:
– Folliculitis
– Dandruff
– Seborrheic dermatitis
– Tinea versicolor
– Jock itch
▪ Reduces itching, flaking, redness, and irritation

Warnings

For external use only

Do not use

▪ On broken or severely damaged skin without consulting a doctor

When Using

▪ Avoid contact with eyes. If contact occurs, rinse thoroughly with water.

Stop Use

▪ Irritation or rash occurs and lasts

Ask Doctor

▪ A known allergy to any of the listed ingredients
▪ Severe skin conditions not diagnosed by a doctor

Keep Out Of Reach Of Children

If swallowed, get medical help or contact a Poison Control Center right away.

Directions

▪ Apply a small amount to the affected area and lather gently.
▪ Leave on for 2–5 minutes before rinsing.
▪ Use 3 to 5 times per week or as directed by a doctor.
▪ For best results, use consistently.

Other information

▪ Store in a cool, dry place away from direct sunlight
▪ Do not use if seal is broken or missing

Inactive ingredients

Aqua (Water), Sodium Laureth Sulfate, Urea, Cetearyl Alcohol, Dimethicone, Cocamidopropyl Betaine, C12-15 Pareth-3, Iodopropynyl Butylcarbamate, Glycol Distearate, Glycol Stearate, Sodium Lauroamphoacetate, Dihydrogenated Tallow Phthalic Acid Amide, Menthol, Piroctone Olamine, Glyceryl, Guar Hydroxypropyltrimonium Chloride, Sodium Chloride, Nymphaea Alba Flower Extract, Coptis Chinensis Extract, Rheum Officinale Extract, Polygonum Multiflorum Root Extract, Houttuynia Cordata Extract, Foeniculum Vulgare Extract, Taraxacum Mongolicum Extract, Panax Ginseng Root Extract, Citric Acid, Disodium EDTA, Salicylic Acid, Melaleuca Alternifolia (Tea Tree) Oil.

Questions

Email us at: cs@pharmbanners.com